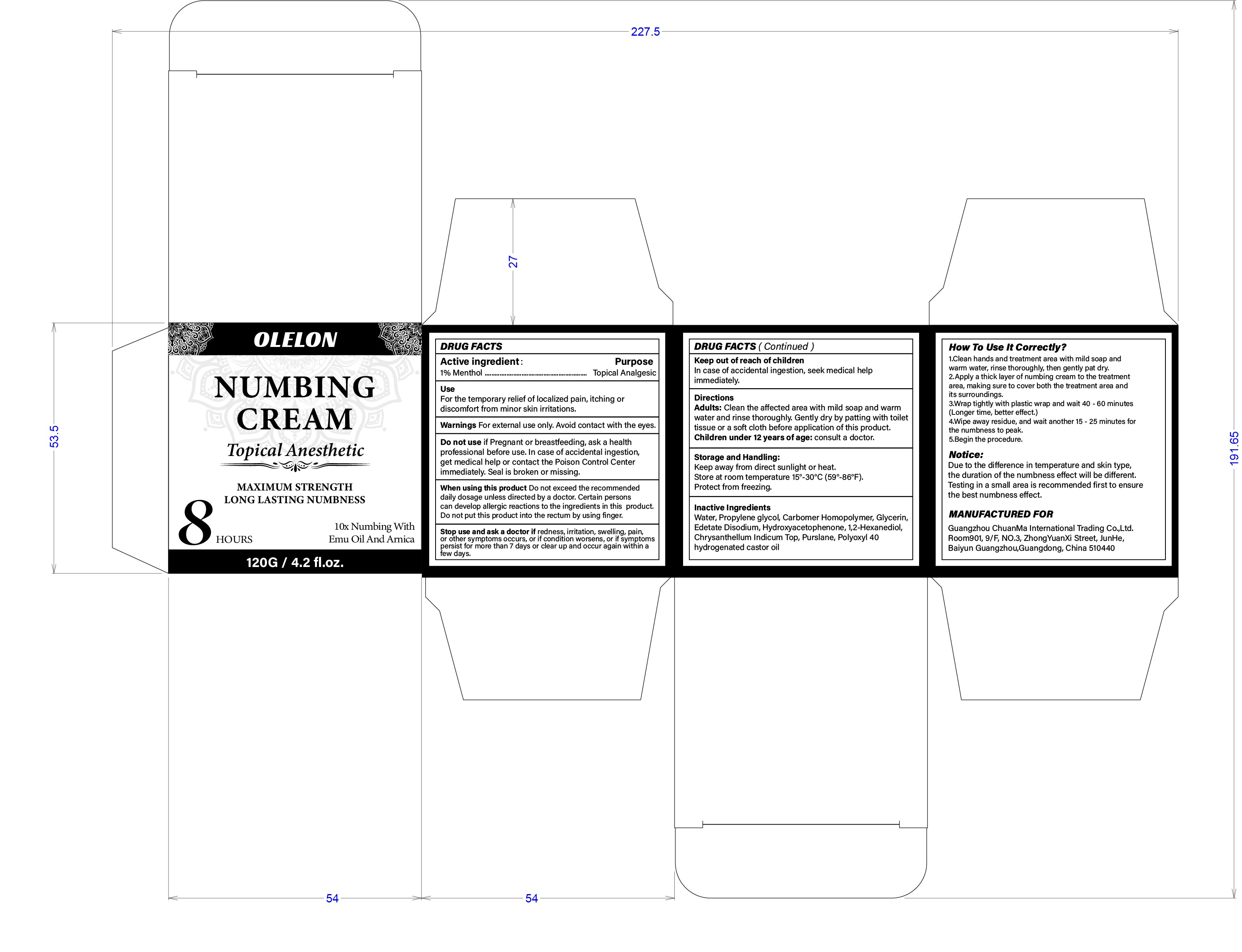 DRUG LABEL: OLELON NUMBING
NDC: 85593-018 | Form: CREAM
Manufacturer: Guangzhou ChuanMa International Trading Co.,Ltd.
Category: otc | Type: HUMAN OTC DRUG LABEL
Date: 20250923

ACTIVE INGREDIENTS: MENTHOL 1 g/100 g
INACTIVE INGREDIENTS: PURSLANE; HYDROXYACETOPHENONE; POLYOXYL 40 HYDROGENATED CASTOR OIL; 1,2-HEXANEDIOL; EDETATE DISODIUM; WATER; CARBOMER HOMOPOLYMER, UNSPECIFIED TYPE; PROPYLENE GLYCOL; GLYCERIN; CHRYSANTHELLUM INDICUM TOP

Active ingredient :

1% Menthol .…
Purpose
Topical Analgesic

PURPOSE

UseFor the temporary relief of localized pain, itching ordiscomfort from minor skin irritations.

WARNINGS

Warnings For external use only. Avoid contact with the eyes.

KEEP OUT OF REACH OF CHILDREN

Keep out of reach of childrenIn case of accidental ingestion, seek medical helpimmediately.

INACTIVE INGREDIENT

Water, Propylene glycol, Carbomer Homopolymer, Glycerin,Edetate Disodium,Hydroxyacetophenone, 1,2-Hexanediol,Chrysanthellum Indicum Top, Purslane, Polyoxyl 40hydrogenated castor oil

INDICATIONS AND USAGE

Directions Adults: Clean the affected area with mild soap and warmwater and rinse thoroughly, Gently dry by patting with toilettissue or a soft cloth before application of this product.Children under 12 years of age: consult a doctor.

DOSAGE AND ADMINISTRATION

1.Clean hands and treatment area with mild soap andwarm water, rinse thoroughly, then gently pat dry.2.Apply a thick layer of numbing cream to the treatmentarea, making sure to cover both the treatment area andits surroundings.3.Wrap tightly with plastic wrap and wait 40 -60 minutes(Longer time, better effect.)4.Wipe away residue, and wait another 15 -25 minutes forthe numbness to peak.
5.Begin the procedure.

When using this product Do not exceed the recommendeddaily dosage unless directed by a doctor. Certain personscan develop allergic reactions to the ingredients in this product.Do not put this product into the rectum by using finger.